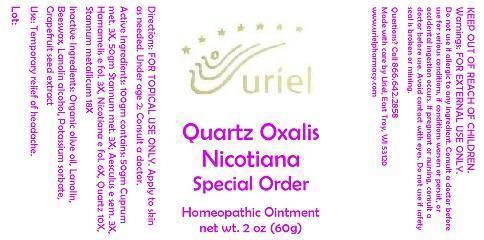 DRUG LABEL: Quartz Oxalis Nicotiana Special Order
NDC: 48951-8272 | Form: OINTMENT
Manufacturer: Uriel Pharmacy Inc.
Category: homeopathic | Type: HUMAN OTC DRUG LABEL
Date: 20140929

ACTIVE INGREDIENTS: COPPER 3 [hp_X]/1 g; TIN 3 [hp_X]/1 g; HORSE CHESTNUT 3 [hp_X]/1 g; HAMAMELIS VIRGINIANA LEAF 3 [hp_X]/1 g; TOBACCO LEAF 6 [hp_X]/1 g; COLLOIDAL SILICON DIOXIDE 10 [hp_X]/1 g
INACTIVE INGREDIENTS: OLIVE OIL; LANOLIN; YELLOW WAX; LANOLIN ALCOHOLS; POTASSIUM SORBATE; CITRUS PARADISI SEED

Quartz Oxalis Nicotiana Special Order

INDICATIONS AND USAGE

Directions: FOR TOPICAL USE ONLY.

DOSAGE AND ADMINISTRATION

Apply to skin as needed. Under age 2: Consult a doctor.

ACTIVE INGREDIENT

Active Ingredients: 100gm contains: 50gm Cuprum met. 3X, 50gm Stannum met. 3X; Aesculus e sem. 3X, Hamamelis e fol. 3X, Nicotiana e fol. 6X, Quartz 10X, Stannum metallicum 18X

INACTIVE INGREDIENT

Inactive Ingredients: Organic olive oil, Lanolin, Beeswax, Lanolin alcohol, Potassium sorbate, Grapefruit seed extract

PURPOSE

Use: Temporary relief of headache.

KEEP OUT OF REACH OF CHILDREN.

WARNINGS

Warnings: FOR EXTERNAL USE ONLY. Do not use if allergic to any ingredient. Consult a doctor before use for serious conditions, if conditions worsen or persist, or accidental ingestion occurs. If pregnant or nursing, consult a doctor before use. Avoid contact with eyes. Do not use if safety seal is broken or missing.

QUESTIONS

Questions? Call 866.642.2858 Made with care by Uriel, East Troy, WI 53120 www.urielpharmacy.com